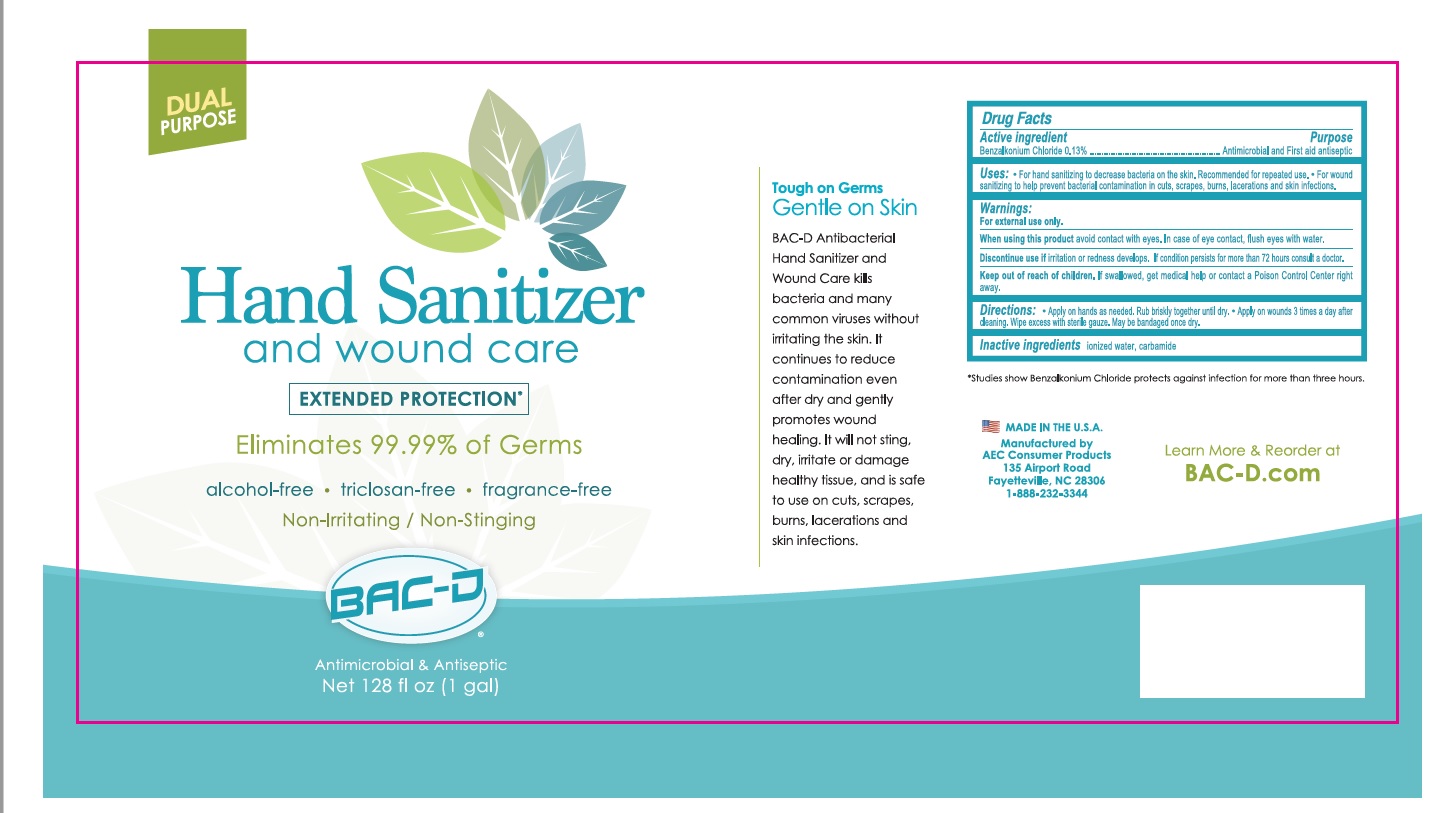 DRUG LABEL: BAC-D
NDC: 86089-600 | Form: LIQUID
Manufacturer: AEC Consumer Products, LLC
Category: otc | Type: HUMAN OTC DRUG LABEL
Date: 20220103

ACTIVE INGREDIENTS: BENZALKONIUM CHLORIDE 0.13 g/100 mL
INACTIVE INGREDIENTS: WATER; UREA

BAC-D Hand And Wound Sanitizer

Active ingredient

Benzalkonium Chloride 0.13%

Purpose

Antimicrobial and First aid antiseptic

Uses:

• For hand sanitizing to decrease bacteria on the skin. Recommended for repeated use. • For wound sanitizing to help prevent bacterial contamination in cuts, scrapes, burns, lacerations and skin infections.

Warnings:

For external use only.

When using this product avoid contact with eyes. In case of eye contact, flush eyes with water.

Discontinue use if irritation or redness develops. If condition persists for more than 72 hours consult a doctor.

Keep out of reach of children. If swallowed, get medical help or contact a Poison Control Center right away.

Directions:

• Apply on hands as needed. Rub briskly together until dry. • Apply on wounds 3 times a day after cleaning. Wipe excess with sterile gauze. May be bandaged once dry.

Inactive ingredients

ionized water, carbamide

DUAL PURPOSE

EXTENDED PROTECTION*

Eliminates 99.99% of Germs

alcohol-free • triclosan-free • fragrance-free

Non-Irritating / Non-Stinging

Antimicrobial & Antiseptic

Tough on Germs

Gentle on skin

BAC-D Antibacterial Hand Sanitizer and Wound Care kills bacteria and many common viruses without irritating the skin. It continues to reduce contamination even after dry and gently promotes wound healing. It will not sting, dry, irritate or damage healthy tissue, and is safe to use on cuts, scrapes, burns, lacerations and skin infections.

*Studies show Benzalkonium Chloride protects against infection for more than three hours.

MADE IN THE U.S.A.

Manufactured by

AEC Consumer Products

135 Airport Road

Fayetteville, NC 28306

Learn more at BAC-D.com

1-888-232-3344